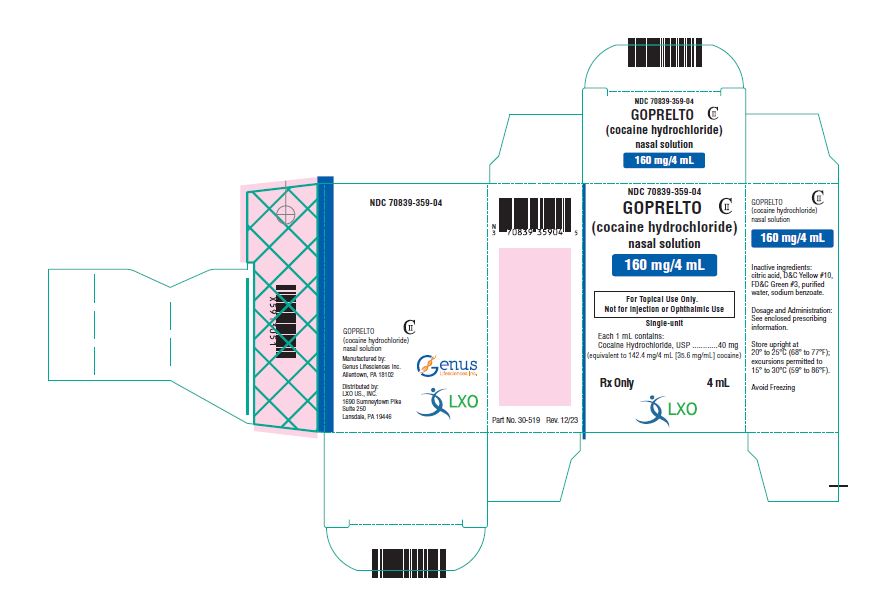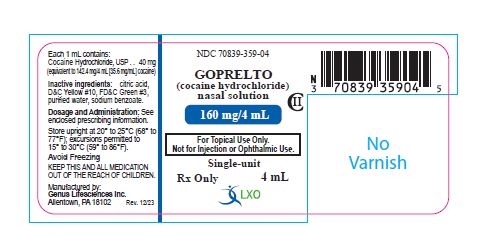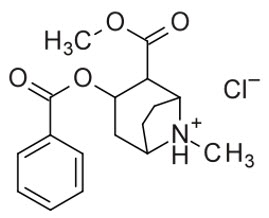 DRUG LABEL: Goprelto
NDC: 70839-359 | Form: SOLUTION
Manufacturer: LXO US Inc.
Category: prescription | Type: HUMAN PRESCRIPTION DRUG LABEL
Date: 20241106
DEA Schedule: CII

ACTIVE INGREDIENTS: COCAINE HYDROCHLORIDE 40 mg/1 mL
INACTIVE INGREDIENTS: FD&C GREEN NO. 3; ANHYDROUS CITRIC ACID; D&C YELLOW NO. 10; WATER; SODIUM BENZOATE

HIGHLIGHTS OF PRESCRIBING INFORMATION

These highlights do not include all the information needed to use GOPRELTO safely and effectively. See full prescribing information for GOPRELTO.
GOPRELTO (cocaine hydrochloride) nasal solution, for intranasal use, CII
Initial U.S. Approval: 2017

WARNING: ABUSE AND DEPENDENCE

See full prescribing information for complete boxed warning.

CNS stimulants, including cocaine hydrochloride, have a high potential for abuse and dependence. (5.1)

1 INDICATIONS AND USAGE

GOPRELTO (cocaine hydrochloride) nasal solution is an ester local anesthetic indicated for the induction of local anesthesia of the mucous membranes when performing diagnostic procedures and surgeries on or through the nasal cavities in adults. (1)

2 DOSAGE AND ADMINISTRATION

• For intranasal use only. (2.1)
• Recommended dose: two pledgets, each containing 40 mg of cocaine hydrochloride,applied to each nasal cavity. (2.2)
• Do not apply to damaged nasal mucosa. (2.1)
• Preparation and Application:
– In a small container, soak four pledgets in the full contents (4 mL) of one bottle of GOPRELTO until the solution is fully absorbed. Each pledget absorbs 1 mL of solution,
equivalent to 40 mg cocaine hydrochloride. (2.2, 2.3)
– Following soaking, place two pledgets in each nasal cavity against the septum. (2.3)
– Leave pledgets in p lace for up to 20 minutes. (2.3)

3 DOSAGE FORMS AND STRENGTHS

Nasal solution: 160 mg/4 mL (40 mg/mL or 4%) cocaine hydrochloride, equivalent to 142.4 mg/4 mL (35.6 mg/mL) cocaine, in a single-unit bottle. (3)

4 CONTRAINDICATIONS

Known hypersensitivity to cocaine hydrochloride, other ester-based anesthetics, or any other component of GOPRELTO. (4)

5 WARNINGS AND PRECAUTIONS

• Seizures: GOPRELTO may lower the convulsive threshold. Monitor patients for development of seizures. (5.2)
• Blood Pressure and Heart Rate Increases: Monitor vital signs, including heart rate and rhythm, in patients after receiving GOPRELTO. Avoid use of GOPRELTO in patients with a recent or active history of uncontrolled hypertension, unstable angina, myocardial infarction, coronary artery disease, or congestive heart failure. (5.3)

6 ADVERSE REACTIONS

The most common adverse reactions (>0.5%) occurring in patients treated with GOPRELTO (cocaine hydrochloride) nasal solution 4% were headache and epistaxis. (6.1)

To report SUSPECTED ADVERSE REACTIONS, contact LXO US., INC. at 1-844-800-8007 or FDA at 1-800-FDA-1088 or www.fda.gov/medwatch.

7 DRUG INTERACTIONS

• Disulfiram: Increases plasma cocaine exposure. Avoid using GOPRELTO in patients taking disulfiram. (7)
• Epinephrine, Phenylephrine: There have been reports of myocardial ischemia, myocardial infarction, and ventricular arrhythmias with concomitant use during nasal surgery. Avoid use of additional vasoconstrictor agents with GOPRELTO. If concomitant use is unavoidable, prolonged vital sign and ECG monitoring may be required. (5.3, 7)

8 USE IN SPECIFIC POPULATIONS

• Pregnancy: May cause fetal harm. (8.1)
• Lactation: Avoid breastfeeding for 48 hours after treatment. (8.2)
• Hepatic Impairment: Monitor for adverse reactions such as headache, epistaxis, and clinically- relevant increases in heart rate or blood pressure. Do not administer a second dose within 24 hours of the first dose. (8.7)

FULL PRESCRIBING INFORMATION

WARNING: ABUSE AND DEPENDENCE

CNS stimulants, including cocaine hydrochloride, have a high potential for abuse and dependence [see Warning and Precautions (5.1). ]

1 INDICATIONS AND USAGE

GOPRELTO (cocaine hydrochloride) nasal solution is indicated for the induction of local anesthesia of the mucous membranes when performing diagnostic procedures and surgeries on or through the nasal cavities in adults.

2 DOSAGE AND ADMINISTRATION

2.1 Important Dosage and Administration Instructions

• GOPRELTO is for intranasal use only.
• Do not apply GOPRELTO to damaged nasal mucosa.

2.2 Dosing Recommendation for Adults

The recommended dose of GOPRELTO is two soaked cottonoid pledgets placed in each nasal cavity, equivalent to 40 mg cocaine hydrochloride per pledget, for a total dose of 160 mg for four pledgets.

The total dose for any one procedure or surgery should not exceed 160 mg, or 3 mg/kg, cocaine hydrochloride. The recommended size of cottonoid pledgets for use with GOPRELTO measure 1.3 cm x 4 cm (sold separately).

2.3 Preparation and Administration of GOPRELTO Pledgets

Pour the full contents of one 4 mL (160 mg) bottle of GOPRELTO into a small container. Soak four cottonoid pledgets until the solution is fully absorbed.
Following soaking, place two pledgets in each nasal cavity against the septum.
Leave pledgets in place for up to twenty minutes. Remove pledgets and continue with the procedure.Discard pledgets and dispose of any unused portion of solution in accordance with institutional procedures for CII products.

3 DOSAGE FORMS AND STRENGTHS

GOPRELTO (cocaine hydrochloride) nasal solution is provided as a 4% solution, 160 mg/4 mL (40 mg/mL), equivalent to 142.4 mg/4 mL (35.6 mg/mL) cocaine, and is a clear, greencolored solution in a single-unit bottle.

4 CONTRAINDICATIONS

GOPRELTO is contraindicated in patients with a known history of hypersensitivity to cocaine hydrochloride, other ester-based anesthetics, or any other component of the product.

5 WARNINGS AND PRECAUTIONS

5.1 Potential for Abuse and Dependence

Central nervous system (CNS) stimulants, including cocaine hydrochloride, have a high potential for abuse and dependence [ see Drug Abuse and Dependence (9.2, 9.3)].

5.2 Seizures

It has been reported in the literature that cocaine hydrochloride may lower the convulsive threshold. The risk may be higher in patients with a history of seizures or in patients with prior electroencephalogram (EEG) abnormalities without seizures, but has been reported in patients with no prior history or EEG evidence of seizures. Monitor patients for development of seizures.

5.3 Blood Pressure and Heart Rate Increases

As reported in the literature, cocaine hydrochloride causes an increase in observed blood pressure and heart rate. In the Phase 3 clinical study with GOPRELTO, increases in blood pressure and heart rate were observed for 60 minutes or longer following pledget removal. Monitor for vital sign changes, including heart rate and rhythm, after administration of GOPRELTO.

Avoid use of GOPRELTO in patients with a recent or active history of uncontrolled hypertension, unstable angina, myocardial infarction, coronary artery disease, or congestive heart failure. Avoid use of additional vasoconstrictor agents such as epinephrine or phenylephrine with GOPRELTO. If concomitant use is unavoidable, prolonged vital sign and ECG monitoring may be required [see Drug Interactions (7)].

5.4 Toxicology Screening

The cocaine hydrochloride in GOPRELTO may be detected in plasma for up to one week after administration. Cocaine hydrochloride and its metabolites may be detected in urine toxicology screening for longer than one week after administration.

6 ADVERSE REACTIONS

6.1 Clinical Trial Experience

Because clinical trials are conducted under widely varying conditions, adverse reaction rates observed in the clinical trials of a drug cannot be directly compared to rates in the clinical trials of another drug and may not reflect the rates observed in practice.

GOPRELTO has been evaluated in four Phase 1 studies and one Phase 3 study, which included 647 adult subjects who received a single topical intranasal 160 mg dose (four pledgets), of GOPRELTO. The randomized, double-blind, controlled Phase 3 study was conducted in adult patients undergoing diagnostic procedures and surgeries on or through the mucous membranes of the nasal cavities, of which 278 received GOPRELTO (4% solution), 275 received cocaine hydrochloride solution 8%, and 95 received placebo. Safety was evaluated for up to 7 days after dosing.

The most commonly reported adverse reactions (>1 patient) to occur in the Phase 3 study with GOPRELTO (4% solution) were headache and epistaxis. Two adverse reactions of headache were severe (Table 1).

No premature discontinuations due to an adverse event, serious adverse events, or deaths were reported in the Phase 3 clinical study.

Table 1: Common Adverse Reactions with GOPRELTO in >1 Patient
System Organ Class / Preferred Term | GOPRELTO 4% (N=278) | Cocaine Hydrochloride Solution 8% (N=275) | Placebo (N=95)
Nervous System Disorders
Headache | 7 (3%) | 4 (2%) | 1 (1%)
Respiratory, Thoracic, and Mediastinal Disorders
Epistaxis | 3 (1%) | 2 (1%) | 0
Psychiatric Disorders
Anxiety | 0 | 2 (1%) | 0

7 DRUG INTERACTIONS

7.1 Disulfiram

Published literature reported that disulfiram treatment increased plasma cocaine exposure, including both AUC and Cmax, by several fold after acute intranasal cocaine administration. Other literature reported that co-administration of disulfiram increased AUC of plasma cocaine by several fold after intravenous cocaine administration [see Clinical Pharmacology (12.3)]. Avoid using GOPRELTO in patients taking disulfiram. Consider using other local anesthetic agents.

7.2 Epinephrine, Phenylephrine

There are reports in the published literature of myocardial ischemia, myocardial infarction, and ventricular arrhythmias after concomitant administration of topical intranasal cocaine with epinephrine and phenylephrine during nasal and sinus surgery.
Avoid use of additional vasoconstrictor agents such as epinephrine and phenylephrine with GOPRELTO during nasal and sinus surgery. If concomitant use is unavoidable, prolonged vital sign and ECG monitoring may be required [see Warnings and Precautions (5.3) ].

7.3 Inhibitors of plasma cholinesterase (pseudocholinesterase)

Cocaine has been described in literature to be primarily metabolized and inactivated by nonenzymatic ester hydrolysis and hepatic carboxylesterase, and also by plasma cholinesterase, hepatic carboxylesterase, and CYP3A4 [see Clinical Pharmacology (12.3)]. The pharmacokinetics of GOPRELTO in patients with reduced plasma cholinesterase activity has not been studied.

Plasma cholinesterase activity may be decreased by chronic administration of certain monoamine oxidase inhibitors, oral contraceptives, or glucocorticoids. It may also be diminished by administration of irreversible plasma cholinesterase inhibitors such as echothiophate, organophosphate insecticides, and certain antineoplastic agents. Patients with reduced plasma cholinesterase (pseudocholinesterase) activity may have reduced clearance and increased exposure of plasma cocaine after administration of GOPRELTO.
Since cocaine is metabolized by multiple enzymes, the effect of reduced plasma cholinesterase activity on cocaine exposure may be limited. No dosage adjustment of GOPRELTO is needed in patients with reduced plasma cholinesterase. Monitor patients with reduced plasma cholinesterase activity for adverse reactions such as headache, epistaxis, and clinically-relevant increases in heart rate or blood pressure.

8 USE IN SPECIFIC POPULATIONS

8.1 Pregnancy

Risk Summary

In animal studies conducted in accordance with good laboratory practices, malformations including vertebral and rib abnormalities were reported when pregnant rabbits were treated with 16 mg/kg cocaine hydrochloride during organogenesis (8 times the adult human exposure following administration of pledgets containing 160 mg of cocaine) and increased pup mortality was noted when pregnant rats were exposed to cocaine hydrochloride during pregnancy at 47 times the adult human AUC exposures. Published rodent studies testing high exposures to cocaine during organogenesis report various malformations at 17 to 34 times the adult human AUC exposures following administration of pledgets containing 160 mg of cocaine.

Data
Human Data

There are no available data on the use of intranasal cocaine hydrochloride solution in pregnant women to inform a drug-associated risk adverse developmental outcomes. There are published data describing adverse developmental outcomes in women with chronic cocaine abuse during pregnancy. The published case-control and observational studies examining the effect of in utero cocaine exposure on fetal growth parameters, after controlling for confounding variables, found exposure was associated with reduced fetal growth compared with non-drugabuse populations. Published data from a large number of studies of women with chronic cocaine abuse during pregnancy are inconsistent in their findings with regard to other developmental outcomes.
Prospective studies controlling for polydrug use (marijuana, alcohol, tobacco) and lifestyle factors, have not demonstrated any association between cocaine abuse and specific major or minor fetal anomalies or other forms of fetal harm (premature birth, stillbirth, miscarriage, low birth weight, reduced head circumference, or placental abruption).

The applicability of the findings from these studies of chronic abuse in pregnancy to a single topical exposure is limited.

Animal Data

No clear evidence of fetal malformations was noted in a study where pregnant rats were treated subcutaneously with up to 30 mg/kg cocaine hydrochloride (48 times the human adult exposure based on AUC following administration of pledgets containing 160 mg of cocaine) from Gestation Day 7 through 17 in the absence of overt maternal rat toxicity. However, a single high-dose fetus was reported with both meningoencephalocele and anophthalmia (unilateral).

Malformations, including vertebral and rib anomalies, were observed when pregnant rabbits were treated subcutaneously with 16 mg/kg cocaine hydrochloride (8 times the human adult exposure based on AUC exposures following administration of pledgets containing 160 mg of cocaine) from Gestation Day 7 through 20. This dose level was associated with evidence of maternal toxicity (convulsions, decreased body weight gain). No adverse effects were noted in animals treated with 8 mg/kg (1.5 times the adult human AUC following administration of pledgets containing 160 mg of cocaine).
An increased incidence of pup mortality between Postnatal Day (PND) 0 to PND 4 and decreased pup body weights from PND 1 to PND 21 were noted when pregnant rats were treated from GD 6 through Lactation Day 20 with 20 mg/kg cocaine hydrochloride (47 times the adult human AUC following administration of pledgets containing 160 mg of cocaine) in the absence of overt maternal toxicity. There was no adverse effect on pre- or postnatal development at 6 mg/kg (7 times the human adult AUC exposure following administration of pledgets containing 160 mg cocaine).

Published studies in pregnant mice suggest that high exposure to cocaine (approximately 17-32 times the adult human AUC following administration of pledgets containing 160 mg of cocaine) produced adverse fetal effects including: exencephaly, cerebral hemorrhage,hydrocephalus, immaturely developed cerebral ventricles, limb anomalies, incomplete bone ossification, hydronephrosis, cryptorchidism, dilated or cystic ureters, and cleft lip/palate.

In a published nonhuman primate study, no adverse effects on physical development or cognitive function were noted after 1 mg/kg cocaine was administered via intramuscular injection three times a day (TID) (approximately 5 times the adult human AUC following administration of pledgets containing 160 mg of cocaine). However, higher exposures to cocaine decreased body weights, overall body length and crown circumference of offspring from pregnant Rhesus monkeys treated with escalating doses up to 7.5 mg/kg cocaine TID intramuscularity per day for 5 days per week from prior to conception to term (39 times the adult human AUC following administration of pledgets containing 160 mg of cocaine).

8.2 Lactation

Risk Summary

Based on limited case reports in published literature, cocaine is present in human milk at widely varying concentrations. Based on its pharmacochemical characteristics, high concentrations of cocaine are expected in breast milk with systemic exposure. The applicability of these findings to a single topical exposure with limited systemic absorption is unclear. No studies have evaluated cocaine concentrations in milk after topical administration of GOPRELTO.

Cocaine is detected in human breastmilk in chronic abuse situations and is expected to be at higher concentrations in milk than in maternal blood based on its physicochemical characteristics. Breastfeeding immediately after administration of GOPRELTO could result in infant plasma concentrations that are approximately half the anticipated maximum maternal plasma concentrations at the clinical dose of 160 mg. The effects of this cocaine plasma concentration in an infant are unknown, but no level of cocaine exposure is considered safe for a breastfed infant.
Adverse reactions have occurred in infants ingesting cocaine through breastmilk, including vomiting, diarrhea, convulsions, hypertension, tachycardia, agitation and irritability. The longterm effects on infants exposed to cocaine through breast milk are unknown. There are no data on the effects of GOPRELTO on milk production.
Because of the potential for serious adverse reactions in breastfed infants, advise nursing women that breastfeeding is not recommended during treatment with GOPRELTO and to pump and discard breastmilk for 48 hours after use of GOPRELTO.

8.4 Pediatric Use

The safety and effectiveness of GOPRELTO in pediatric patients (17 years of age and younger) has not been evaluated.

Animal Data

Adverse CNS-related clinical signs within the first several days of dosing and decreased body weights were observed when juvenile rat pups were dosed subcutaneously with 25 mg/kg cocaine hydrochloride (15 and 32 times the adult human AUC exposure following administration of pledgets containing 160 mg of cocaine for males and females, respectively) from PND 7 to PND 28. No adverse effects were noted in pups dosed with 12.5 mg/kg (7 times the adult human AUC exposure following administration of pledgets containing 160 mg of cocaine).
A single mortality (male) and transient CNS signs were observed in male and female juvenile rat pups that were dosed subcutaneously up to 25 mg/kg cocaine hydrochloride (113 times the adult human AUC exposure) from PND 28 to PND 56. No adverse effects were noted in male pups dosed with 12.5 mg/kg or female pups dosed with 25 mg/kg (84 and 117 times the adult human AUC exposure following administration of pledgets containing 160 mg of cocaine respectively).

8.5 Geriatric Use

Of the total number of subjects in the Phase 3 study, 12.1% of those who received GOPRELTO were 65 and over. No overall differences in safety or effectiveness were observed between these subjects and younger subjects, and other reported clinical experience and pharmacokinetic data [see Clinical Pharmacology (12.3)] has not identified differences in responses between the elderly and younger patients, but greater sensitivity of some older individuals cannot be ruled out.

8.6 Renal Impairment

No dosage adjustment of GOPRELTO is needed in patients with mild, moderate, or severe renal impairment [ see Clinical Pharmacology (12.3)].

8.7 Hepatic Impairment

No dosage adjustment of GOPRELTO is needed in patients with hepatic impairment. Monitor patients with hepatic impairment for adverse reactions such as headache, epistaxis, and clinically- relevant increases in heart rate or blood pressure and do not administer a second dose of GOPRELTO to these patients within 24 hours of the first dose [ see Clinical Pharmacology (12.3)].

8.8 Patients with Reduced Plasma Cholinesterase Activity

Cocaine has been described in literature to be primarily metabolized and inactivated by nonenzymatic ester hydrolysis and hepatic carboxylesterase, and also by plasma cholinesterase, hepatic carboxylesterase and CYP3A4 [see Clinical Pharmacology (12.3)]. Pharmacokinetics of GOPRELTO in patients with reduced plasma cholinesterase activity has not been studied.

Genetic abnormalities of plasma cholinesterase (e.g., patients who are heterozygous or homozygous for atypical plasma cholinesterase gene), disease conditions such as malignant tumors, severe liver or kidney disease, decompensated heart disease, infections, burns, anemia, peptic ulcer, or myxedema or other physiological states such as pregnancy may lead to reduced plasma cholinesterase activity. Patients with reduced plasma cholinesterase (pseudocholinesterase) activity may have reduced clearance and increased exposure of plasma cocaine after administration of GOPRELTO.

Since cocaine is metabolized by multiple enzymes, the effect of reduced plasma cholinesterase activity on cocaine exposure may be limited. No dosage adjustment of GOPRELTO is needed in patients with reduced plasma cholinesterase. Monitor patients with reduced plasma cholinesterase activity for adverse reactions such as headache, epistaxis, and clinically-relevant increases in heart rate or blood pressure.

9 DRUG ABUSE AND DEPENDENCE

9.1 Controlled Substance

GOPRELTO contains cocaine, a Schedule II controlled substance.

9.2 Abuse

GOPRELTO contains cocaine, a substance with a high potential for abuse. GOPRELTO can be misused and abused, which can lead to addiction. GOPRELTO may also be diverted for abuse purposes [ see Warnings and Precautions (5.1)].

Drug abuse is the intentional non-therapeutic use of a prescription drug, even once, for its rewarding psychological or physiological effects. Drug addiction is a cluster of behavioral, cognitive, and physiological phenomena that develop after repeated substance use and includes: a strong desire to take the drug, difficulties in controlling its use, persisting in its use despite harmful consequences, a higher priority given to drug use than to other activities and obligations, increased tolerance, and sometimes a physical withdrawal. Drug abuse of a substance may occur without progression to drug addiction. “Drug-seeking” behavior is very common in persons with substance use disorders.
Drug abuse and addiction are conditions that are separate and distinct from physical dependence and tolerance [see Dependence (9.3)]. Health care providers should be aware that abuse and addiction may occur in the absence of symptoms indicative of physical dependence and tolerance.
Individuals who abuse stimulants may use GOPRELTO for abuse purposes. Adverse events associated with abuse of cocaine include euphoria, excitation, irritability, restlessness, anxiety, paranoia, confusion, headache, psychosis, hypertension, stroke, seizures, dilated pupils, nausea, vomiting, and abdominal pain. Intranasal abuse can produce damage to the nostrils (e.g.,ulceration and deviated septum). Abuse of cocaine can result in overdose, convulsions, unconsciousness, coma, and death [ see Overdosage (10)]. Parenteral drug abuse is commonly associated with transmission of infectious diseases such as hepatitis and HIV.

GOPRELTO, like all prescription drugs with abuse potential, can be diverted for non-medical use into illicit channels of distribution. In order to minimize these risks, effective accounting procedures should be implemented, in addition to routine procedures for handling controlled substances.

9.3 Dependence

Physical dependence is a state that develops as a result of physiological adaptation in response to repeated drug use, manifested by withdrawal signs and symptoms after abrupt discontinuation or a significant dose reduction of a drug. GOPRELTO is approved for topical single use during diagnostic procedures and surgeries, so physical dependence and withdrawal symptoms are unlikely to develop. Although GOPRELTO is not indicated for chronic therapy, repeated misuse or abuse of this product may lead to physical dependence.

10 OVERDOSAGE

No cases of overdose with GOPRELTO were reported in clinical trials. Blood pressure and heart rate increases were greater with cocaine hydrochloride solution 8% than with GOPRELTO. In the case of an overdose, consult with a certified poison control center (1-800-222-1222) for up-to-date guidance and advice for treatment of overdosage. Individual patient response to cocaine varies widely. Toxic symptoms may occur idiosyncratically at low doses. Manifestations of cocaine overdose associated with illicit use of cocaine reported in literature and based on reports in FDA’s Adverse Events Reporting System (AERS) database include death, cardio-respiratory arrest, cardiac arrest, respiratory arrest, tachycardia, myocardial infarction, agitation, aggression, restlessness, tremor, hyperreflexia, rapid respiration, confusion, assaultiveness, hallucinations, panic states, hyperpyrexia, and rhabdomyolysis. Fatigue
and depression usually follow the central nervous system stimulation. Other reactions include arrhythmias, hypertension or hypotension, circulatory collapse, nausea, vomiting, diarrhea, and abdominal cramps. Fatal poisoning is usually preceded by convulsions and coma. Because cocaine is significantly distributed to tissues and rapidly metabolized, dialysis and hemoperfusion are not effective. Acidification of the urine does not significantly enhance cocaine elimination.

11 DESCRIPTION

GOPRELTO (cocaine hydrochloride) nasal solution for intranasal use contains a 4% solution, 160 mg/4 mL (40 mg/mL), equivalent to 142.4 mg/4 mL (35.6 mg/mL) cocaine, an ester local anesthetic.
The chemical name for cocaine hydrochloride is (1R,2R,3S,5S) methyl 3-(benzoyloxy)-8- methyl-8-azabicyclo[3.2.1]octane-2-carboxylate hydrochloride. The molecular formula is C17H21NO4•HCl and the molecular weight is 339.81. The structural formula is:

Inactive ingredients are anhydrous citric acid, D&C Yellow No. 10, FD&C Green No. 3, sodium benzoate, and purified water.

12 CLINICAL PHARMACOLOGY

12.1 Mechanism of Action

Cocaine hydrochloride is a local anesthetic of the ester type. Cocaine hydrochloride prevents conduction in nerve fibers by reversibly blocking sodium channels and preventing the transient rise in sodium conductance necessary for generation of an action potential.

12.2 Pharmacodynamics

Cardiac Electrophysiology

The effect of GOPRELTO (cocaine hydrochloride) nasal solution on the QTc interval was evaluated in a randomized, positive- and placebo-controlled four-period crossover thorough QTc study in 24 healthy subjects. No clinically relevant QTc prolongation was observed at the highest clinically relevant concentrations with a single therapeutic dose.

12.3 Pharmacokinetics

Absorption
The pharmacokinetics of GOPRELTO (cocaine hydrochloride) nasal solution have been assessed in 74 healthy adult subjects across 4 studies. Following intranasal application of two 40 mg pledgets applied to each nasal cavity (160 mg cocaine hydrochloride total dose) for 20 minutes, the geometric mean (SD) cocaine Cmax was 43.2 (1.73) ng/mL. The median (range) time to peak plasma concentration (tmax) was 0.42 (0.25 – 1.75) hours after pledget application.

Distribution
Cocaine has been described in literature as approximately 84 – 92% bound to human plasma proteins, binding primarily to alpha-1-acid glycoprotein (AAG) and albumin.
In studies with GOPRELTO, the apparent volume of distribution (Vd/F) of cocaine after intranasal administration is 3,877 ± 1,266 L.

Elimination

Metabolism
Cocaine has been described in literature to be primarily metabolized and inactivated by nonenzymatic ester hydrolysis and hepatic carboxylesterase 1 to form benzoylecgonine (BE), and by plasma cholinesterase and hepatic carboxylesterase 2 to form ecgonine methyl ester (EME). In human liver microsomes, cocaine undergoes CYP3A4 mediated N-demethylation to produce a minor metabolite, norcocaine, which is pharmacologically active.

Excretion
Cocaine has been described in literature to be primarily eliminated by biotransformation to inactive metabolites, BE and EME. Less than 10% of the administered dose is excreted unchanged in the urine. BE and EME are both predominantly excreted by the kidneys.

In studies with GOPRELTO, 0-32 hour urinary recoveries of cocaine, BE, and EME as a percentage of dose were approximately 0.1%, 2.0%, and 1.0%, respectively. The mean elimination half-life of cocaine was 1.0 to 1.7 hours; with longer plasma sampling (32 hours) and a highly sensitive assay, mean half-life values of 5.0 to 8.0 hours were observed at very low plasma concentrations.

The apparent clearance of cocaine after intranasal administration of GOPRELTO (CL/F) is 3096 ± 1276 L/h.

Specific Populations

In studies with GOPRELTO, cocaine exposure (i.e., Cmax, AUClast, and AUCinf) was slightly higher in females than males whereas tmax and half-life were similar in males and females. GOPRELTO pharmacokinetics are not affected by age or weight.

Renal Impairment
In a pharmacokinetic study of GOPRELTO in subjects with normal and severe renal impairment (eGFR 15-29 mL/min/1.73 m2), mean AUC and Cmax were slightly higher in subjects with severe renal impairment compared to those with normal renal function and clearance was slightly lower [see Use in Specific Populations (8.6)].

Hepatic Impairment
In a pharmacokinetic study of GOPRELTO in subjects with normal, Child-Pugh Class B, and Child-Pugh Grade C hepatic impairment, there was a minimal effect of hepatic impairment on cocaine Cmax. In moderately impaired subjects (n=9) there was a higher than two-fold increase in AUC (79.2 ng.h/mL in normal subjects to 225 ng.h/mL in Child-Pugh Grade B subjects) and the clearance was reduced by more than half (1735 L/h in normal 629 L/h in Child-Pugh Grade B subjects). In severely impaired subjects (n=3) there was an eighty percent increase in AUC (79.2 ng.h/mL in normal subjects to 142 ng.h/mL in Child-Pugh Grade C subjects) and the clearance was reduced to half (1735 L/h in normal 959 L/h in Child-Pugh Grade C subjects) [see Use in Specific Populations (8.7)].

Drug Interaction Studies
Cocaine has been found to be a CYP2D6 inhibitor in in-vitro studies employing human liver microsomes. In vitro transporter inhibition studies also found cocaine to be an inhibitor of OCT2. However, the relatively low plasma concentrations of cocaine resulting from therapeutic doses of GOPRELTO are not expected to raise significant drug-drug interaction concerns.

Disulfiram
It has been reported in the published literature that disulfiram treatment increased plasma cocaine exposure, including both AUC and Cmax, by several fold after acute intranasal cocaine administration. Other published literature reported that co-administration of disulfiram increased AUC of plasma cocaine by several fold after intravenous cocaine administration [see Drug Interactions (7.1)].

13 NONCLINICAL TOXICOLOGY

13.1 Carcinogenesis, Mutagenesis, Impairment of Fertility

Carcinogenesis
Long-term animal studies to evaluate the carcinogenic potential of cocaine have not been conducted.

Mutagenesis
In published studies, cocaine was genotoxic in the in vitro chromosomal aberration assay, the in vitro sister chromatid exchange assay, the in vitro micronucleus assay, and the in vitro hypoxanthine-guanine phosphoribosyltransferase (hgprt) assay. Cocaine was equivocal in a published in vivo micronucleus assay and the in vivo comet assay (liver). Cocaine was not mutagenic in the in vitro bacterial reverse mutation assay (Ames assay).

Impairment of Fertility

No adverse effects on fertility or early embryonic development were reported in a study where male rats were administered up to 20 mg/kg cocaine hydrochloride via subcutaneous injection for 28 days prior to mating and female rats were treated with the same dose for 14 days prior to mating through Gestation Day 7. The 20 mg/kg/dose resulted in AUC exposures that were 31 times (males) and 47 times (females) the adult human AUC following administration of pledgets containing 160 mg of cocaine.

14 CLINICAL STUDIES

A double-blind, multicenter, single-dose, placebo- and dose-controlled, parallel-group study was conducted in 648 subjects undergoing diagnostic procedures and surgeries on or through the mucous membranes of the nasal cavities. Subjects were randomized to receive GOPRELTO (n=278), cocaine hydrochloride solution 8% (n=275), to explore the dosing range, or placebo (n=95). Nasal endoscopy, nasal laryngoscopy, nasopharyngeal laryngoscopy, and nasal debridement comprised 88% of all procedures performed in the GOPRELTO group and 85% of all procedures performed in the placebo group. All subjects completed the diagnostic or surgical procedure.

In the GOPRELTO group, two 40 mg pledgets were applied to the septum in each nasal cavity (160 mg cocaine hydrochloride total dose) and left in place for up to 20 minutes. Similarly, pledgets were applied in the placebo group. Topical anesthesia was assessed using the visual numeric rating scale (VNRS) during a von Frey Filament test prior to the diagnostic procedure or surgery. After subject-reported pain scores were collected, the blind to placebo was broken and placebo subjects were provided the option of receiving anesthesia. The primary efficacy endpoint was analgesic success, defined in the GOPRELTO group as a subject-reported pain score of 0 (no pain) on the VNRS during the von Frey Filament test, and no additional anesthetic or analgesic medication administration during the diagnostic procedure or surgery. Analgesic success was defined in the placebo group as a subject-reported pain score of 0 on the VNRS during the von Frey Filament test. Subjects did not receive supplemental intravenous sedation or general anesthesia during the study.

Table 2 provides the efficacy results for the primary endpoint of analgesic success showing a significant difference in the analgesic success rate between placebo and GOPRELTO.

Table 2: Analgesic Success
Event | GOPRELTO (N=278) n (%) | Placebo (N=95) n (%)
Success | 215 (77%) | 14 (15%)
Failure | 63 (23%) | 81 (85%)

Of the 63 (23%) failures in the GOPRELTO group, 4 subjects requested additional anesthetic medication. Of these 4 subjects, 1 subject reported 0 on the VNRS during the von Frey Filament test. Of the 81 (85%) failures in the placebo group, 50 subjects required additional anesthetic medication.

16 HOW SUPPLIED/STORAGE AND HANDLING

GOPRELTO (cocaine hydrochloride) nasal solution is a clear, green colored liquid available as one dosage strength:
160 mg/4 mL (40 mg/mL or 4%) cocaine hydrochloride, equivalent to 142.4 mg/4 mL (35.6 mg/mL) cocaine
NDC # 70839-359-04: Single-unit 4 mL bottle
Store upright at 20° to 25°C (68° to 77°F); excursions permitted to 15° to 30°C (59° to 86°F)
[ see USP, Controlled Room Temperature (CRT)]. Avoid freezing.

17 PATIENT COUNSELING INFORMATION

Potential for Abuse and Dependence
Advise patients that GOPRELTO is a controlled substance and it can be abused and lead to dependence [see Warnings and Precautions (5.1), Drug Abuse and Dependence (9)].
Toxicology Screening
Advise patients that the cocaine hydrochloride in GOPRELTO may be detected in plasma for up to one week after administration. Cocaine hydrochloride and its metabolites may be detected in urine toxicology screening for longer than one week after administration. [ see Warnings and Precautions (5.4)].
Seizures
Advise patients that GOPRELTO may lower the seizure threshold. Patients should be monitored for development of seizures. [ see Warnings and Precautions (5.2) ].
Blood Pressure and Heart Rate Increase
Advise patients that GOPRELTO can cause increases in blood pressure and heart rate and should be avoided in patients with recent or active history of uncontrolled hypertension, unstable angina, myocardial infarction, coronary artery disease, or congestive heart failure [ see Warnings and Precautions (5.3) ].

Headache and/or Epistaxis

Inform patients that headache and/or epistaxis are the most frequently experienced side effects that should resolve without treatment. Instruct patients to contact their health care professional if these symptoms persist [ see Adverse Reactions (6) ].

Pregnancy
Inform female patients of reproductive potential that GOPRELTO may cause fetal harm and to inform their prescriber of a known or suspected pregnancy [ see Use in Specific Populations (8.1)] .
Lactation
Advise a nursing woman that breastfeeding is not recommended during treatment with GOPRELTO and to pump and discard breastmilk for 48 hours after administration of GOPRELTO nasal solution [ see Use in Specific Populations (8.2) ]

Manufactured by:

Genus Lifesciences Inc.
514 North 12th Street
Allentown, PA 18102

Distributed by:
LXO US, INC.
1690 Sumneytown Pike
Suite 250
Lansdale, PA 19446

PACKAGE LABEL

NDC 70839-359-04

GOPRELTO
CII
(cocaine hydrochloride)
nasal solution

160 mg/4 mL

For Topical Use Only.
Not for Injection or Ophthalmic Use

Single-unit

Each 1 mL contains:
Cocaine Hydrochloride, USP 40 mg
(equivalent to 142.4 mg/4 mL [35.6 mg/mL] cocaine)

Rx Only
4 mL

LXO US Inc.